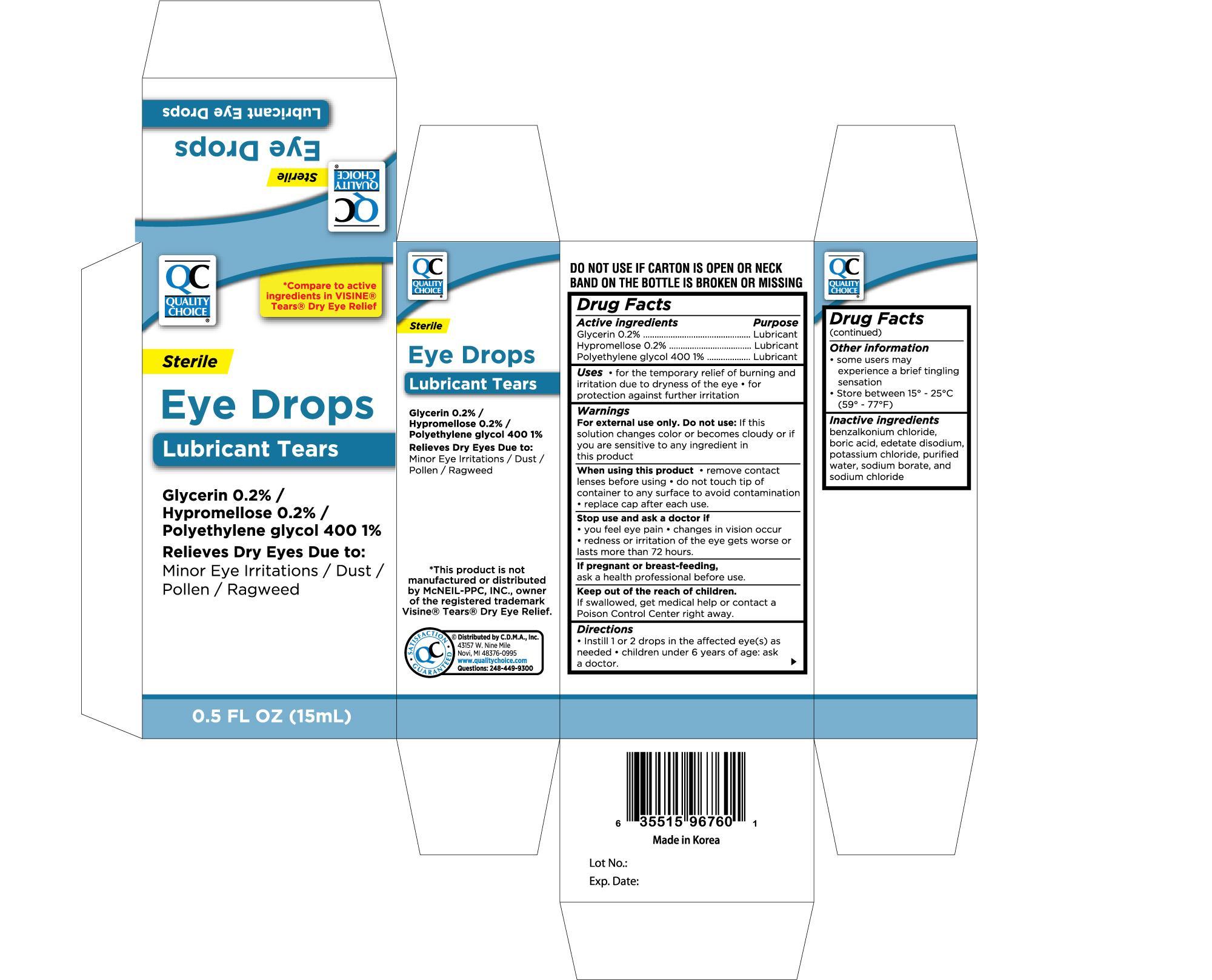 DRUG LABEL: QUALITY CHOICE LUBRICANT TEARS EYE 
NDC: 63868-967 | Form: SOLUTION/ DROPS
Manufacturer: CHAIN DRUG MARKETING ASSOCIATION INC
Category: otc | Type: HUMAN OTC DRUG LABEL
Date: 20120930

ACTIVE INGREDIENTS: GLYCERIN 2 mg/1 mL; HYPROMELLOSES 2 mg/1 mL; POLYETHYLENE GLYCOL 400 10 mg/1 mL
INACTIVE INGREDIENTS: BENZALKONIUM CHLORIDE; BORIC ACID; EDETATE DISODIUM; POTASSIUM CHLORIDE; SODIUM BORATE; SODIUM CHLORIDE; WATER

Drug Facts

Active ingredients Purpose

Glycerin 0.2%..................................................................................Lubricant

Hypromellose 0.2%..........................................................................Lubricant

Polyethylene glycol 400 1%..............................................................Lubricant

Uses

- for the temporary relief of burning and irritation due to dryness of the eye
- for protection against further irritation

Warnings

For external use only.

Do not use:

- if this solution changes color or becomes cloudy or if you are sensitive to any ingredient in this product

When using this product

- remove contact lenses before use
- do not use if this solution changes color or becomes cloudy
- do not touch tip of container to any surface to avoid contamination
- replace cap after each use

Stop use and ask a doctor if

- you feel eye pain
- changes in vision occur
- redness or irritation of the eye lasts
- condition worsens or lasts more than 72 hours

If pregnant or breast-feeding,

ask a health professional before use.

Keep out of reach of children. If swallowed, get medical help or contact a Poison Control Center right away

Directions

- Instill 1 or 2 drops in the affected eye(s) as needed.
- children under 6 years of age: ask a doctor

Other information

- some users may experience a brief tingling sensation
- store at 15o to 25oC (59o to 77oF)

Inactive ingredients

benzalkonium chloride, boric acid, dextrose, glycine, magnesium chloride, potassium chloride, purified water, sodium borate, sodium chloride, sodium citrate, sodium lactate.

DOSAGE AND ADMINISTRATION

Distributed by C.D.M.A., Inc.

43157 W. Nine Mile

Novi, MI 48376-0995

www.qualitychoice.com

Made in Korea